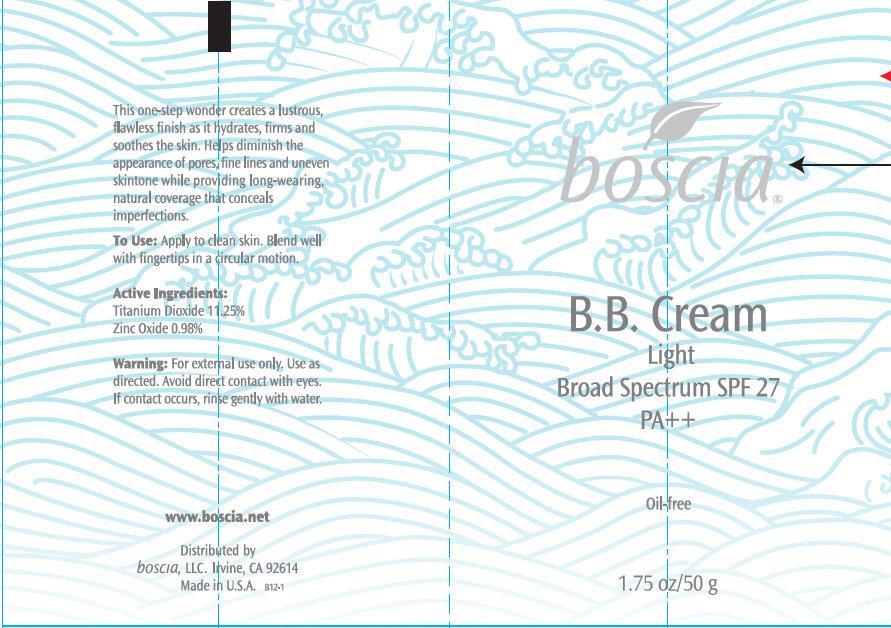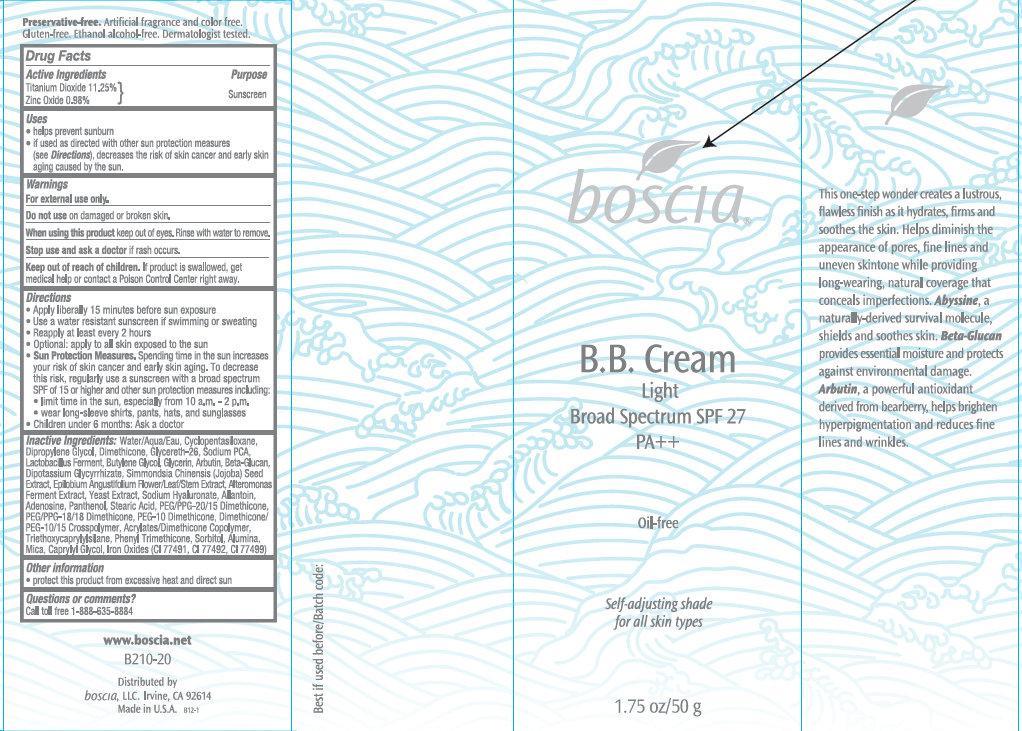 DRUG LABEL: Boscia B.B. LIGHT Broad Spectrum SPF 27 PA Self-Adjusting Shade
NDC: 76151-231 | Form: CREAM
Manufacturer: Boscia LLC
Category: otc | Type: HUMAN OTC DRUG LABEL
Date: 20231212

ACTIVE INGREDIENTS: TITANIUM DIOXIDE 11.25 g/100 g; ZINC OXIDE 0.98 g/100 g
INACTIVE INGREDIENTS: FERRIC OXIDE RED; WATER; CYCLOMETHICONE 5; DIPROPYLENE GLYCOL; GLYCERETH-26; SODIUM PYRROLIDONE CARBOXYLATE; BUTYLENE GLYCOL; GLYCERIN; ARBUTIN; SIMMONDSIA CHINENSIS SEED; EPILOBIUM ANGUSTIFOLIUM FLOWERING TOP; YEAST; ALLANTOIN; ADENOSINE; PANTHENOL; STEARIC ACID; PEG/PPG-20/15 DIMETHICONE; TRIETHOXYCAPRYLYLSILANE; PHENYL TRIMETHICONE; SORBITOL; ALUMINUM OXIDE; MICA; CAPRYLYL GLYCOL

Boscia B.B. Cream LIGHT Broad Spectrum SPF 27 PA Oil-Free Self-Adjusting Shade

Active Ingredients

Titanium Dioxide 11.25% Zinc Oxide 0.98%

Purpose

Sunscreen

Uses

- helps prevent sunburn

- if used as directed with other sun protection measures (), decreases the risk of skin cancer and early skin aging caused by the sun. see Directions

Warnings

For external use only.

Do not use

on damaged or broken skin.

When using this product

keep out of eyes. Rinse with water to remove.

Stop use and ask a doctor

if rash occurs.

Keep out of reach of children.

If product is swallowed, get medical help or contact a Poison Control Center right away.

Directions

- Apply liberally 15 minutes before sun exposure
- Use a water resistant sunscreen, if swimming or sweating
- Reapply at least every 2 hours
- Optional: apply to all skin exposed to the sun.
- . Spending time in the sun increases your risk of skin cancer and early skin aging. To decrease this risk, regularly use a sunscreen with a broad spectrum SPF of 15 or higher and other sun protection measures including: Sun Protection Measures
- limit time in the sun, especially from 10 a.m - 2 p.m
- wear long-sleeve shirts, pants, hats, and sunglasses
- Children under 6 months: Ask a doctor

Inactive Ingredients

Water/Aqua/Eau, Cyclopentasiloxane, Dipropylene Glycol, Dimethicone, Glycereth-26, Sodium PCA, Lactobacillus Ferment, Butylene Glycol, Glycerin, Arbutin, Beta-Glucan, Dipotassium Glycyrrhizate, Simmondsia Chinensis (Jojoba) Seed Extract, Epilobium Angustifolium Flower/Leaf/Stem Extract, Alteromonas Ferment Extract, Yeast Extract, Sodium Hyaluronate, Allantoin, Adenosine, Panthenol, Stearic Acid, PEG/PPG 20/15 Dimethicone, PEG/PPG-18/18 Dimethicone, PEG-10 Dimethicone, Dimethicone PEG-10/15 Crosspolymer, Acrylate/Dimethicone Copolymer, Triethoxycaprylylsilane, Phenyl Trimethicone, Sorbitol, Alumina, Mica, Caprylyl Glycol, Iron Oxide (CI 77491, CI77492, CI77499)

Other information

- protect this product from excessive heat and direct sun

Questions or comments ?

Call toll free 1-888-635-8884

This one-step wonder creates a lustrous, flawless finish as it hydrates, firms and soothes the skin. Helps diminish the appearance of pores, fine lines and uneven skintone while providing long-wearing, natural coverage that conceals imperfections. , a naturally-derived survival mollucule. shields and soothes skin. provides essential moisture and protects against environmental damage. , a powerful antioxidant derived from bearberry, helps brighten hyperpigmentation and reduces fine lines and wrinkles. . Artificial fragrance and color free. Gluten-free. Ethanol alcohol-free. Dermatologist tested. B210-20 Distributed by boscia, LLC. Irvine, CA 92614 Made in U.S.A e Abyssin Beta-Glucan Arbutin Preservative-freewww.boscia.net

PACKAGE LABEL

boscia B.B. Cream Light Broad Spectrum SPF 27 PA++ Oil-free Self-adjusting shade for all skin types 1.75oz/50 g